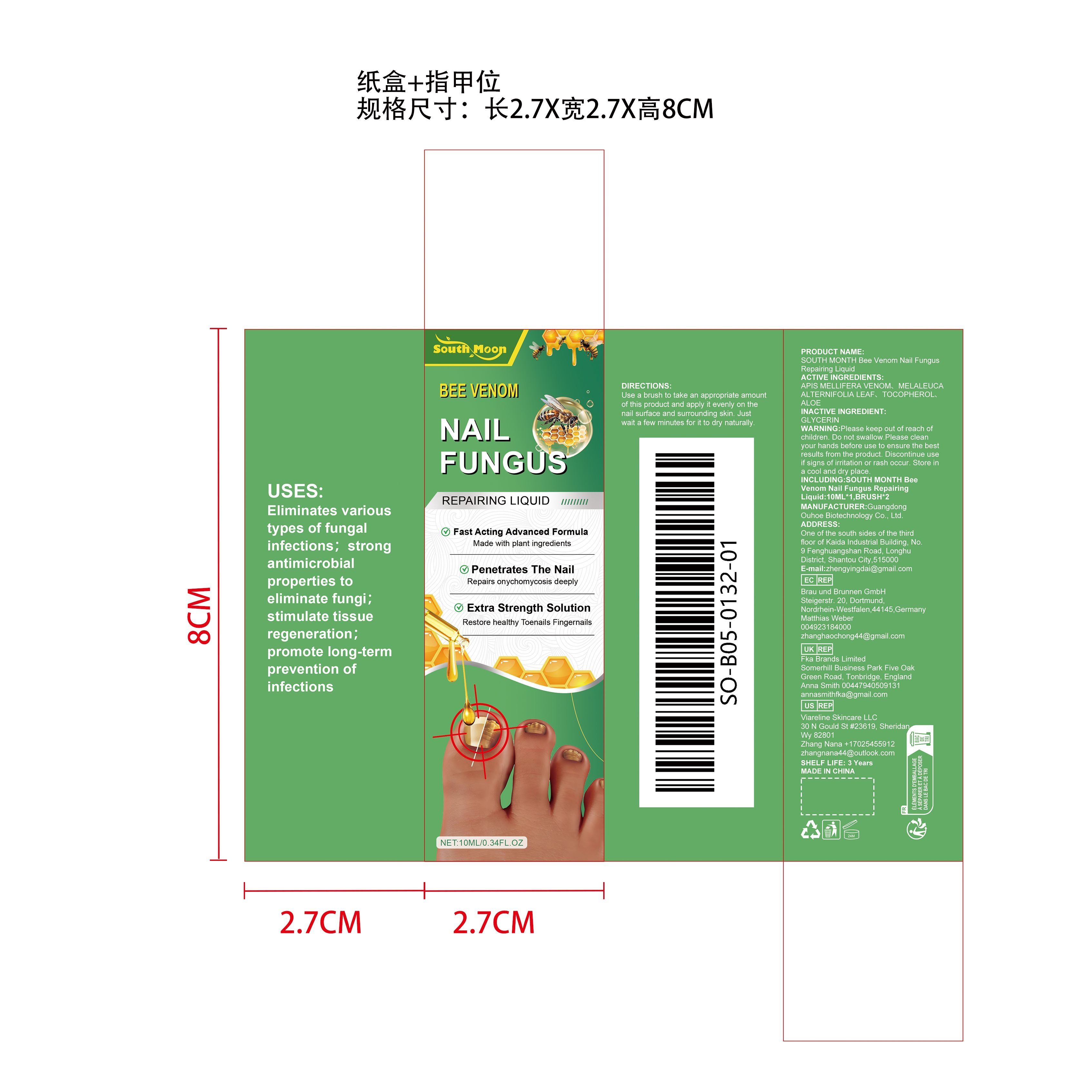 DRUG LABEL: SOUTH MONTH Bee Venom Nail Fungus Repairing Liquid
NDC: 84744-063 | Form: LIQUID
Manufacturer: Guangdong Ouhoe Biotechnology Co., Ltd.
Category: otc | Type: HUMAN OTC DRUG LABEL
Date: 20241024

ACTIVE INGREDIENTS: MELALEUCA ALTERNIFOLIA LEAF 1 mg/10 mg; TOCOPHEROL 1.5 mg/10 mg; APIS MELLIFERA VENOM 3 mg/10 mg; ALOE 1.5 mg/10 mg
INACTIVE INGREDIENTS: GLYCERIN 3 mg/10 mg

ACTIVE INGREDIENTS

APIS MELLIFERA VENOM、MELALEUCA ALTERNIFOLIA LEAF、TOCOPHEROL、ALOE

purpose

Eliminates various types of fungal infections; strong antimicrobial properties to eliminate fungi; stimulate tissue regeneration; promote long-term prevention of infections

use

Use a brush to take an appropriate amount of this product and apply it evenly on the nail surface and surrounding skin. Just wait a few minutes for it to dry naturally.

WARNINGS

Please keep out of reach of children. Do not swallow.Please clean your hands before use to ensure the best results from the product. Discontinue use if signs of irritation or rash occur. Store in a cool and dry place.

KEEP OUT OF REACH OF CHILDREN

Please keep out of reach of children. Do not swallow.

STOP USE

Discontinue use if signs of irritation or rash occur.

DO NOT USE

Discontinue use if signs of irritation or rash occur.

STORAGE AND HANDLING

Store in a cool and dry place.

INACTIVE INGREDIENT

GLYCERIN